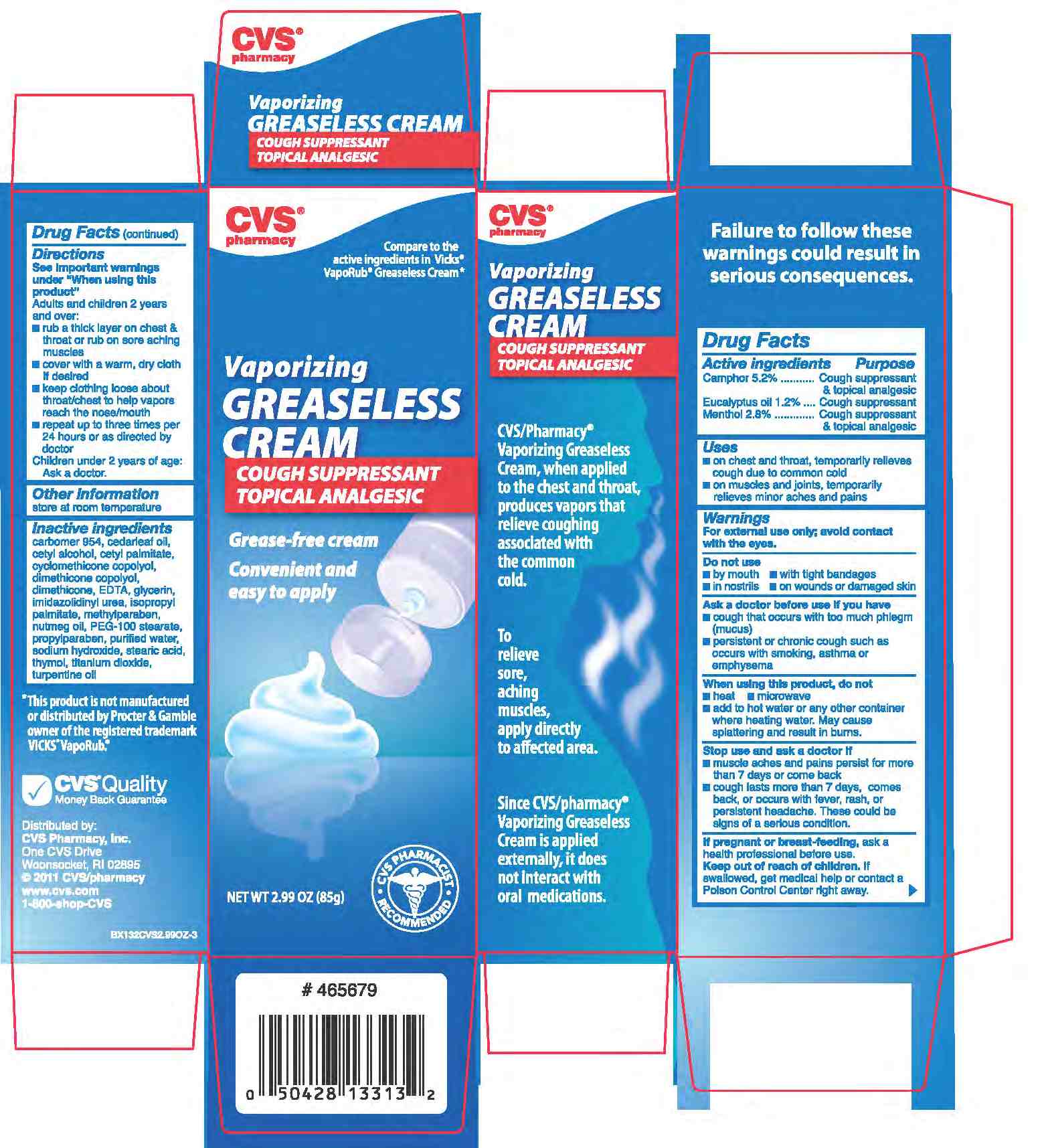 DRUG LABEL: CAMPHOR, EUCALYPTUS OIL and MENTHOL
NDC: 59779-717 | Form: OINTMENT
Manufacturer: CVS
Category: otc | Type: HUMAN OTC DRUG LABEL
Date: 20110214

ACTIVE INGREDIENTS: CAMPHOR (SYNTHETIC) 52 mg/1 mL; EUCALYPTUS OIL 12 mg/1 mL; MENTHOL 28 mg/1 mL
INACTIVE INGREDIENTS: WATER; CARBOMER 934; CETYL ALCOHOL; CEDAR LEAF OIL; CETYL PALMITATE; CYCLOMETHICONE 5; DIMETHICONE; GLYCERIN; DIAZOLIDINYL UREA; ISOPROPYL PALMITATE; METHYLPARABEN; NUTMEG OIL; POLYOXYL 100 STEARATE; PROPYLPARABEN; SODIUM HYDROXIDE; STEARIC ACID; STEARYL ALCOHOL; THYMOL; TITANIUM DIOXIDE; TURPENTINE

drug facts

Active ingredient Purpose
Camphor 5.2%.............................Cough Suppressant and topical analgesic
Eucalyptus oil 1.2%......................Cough Suppressant
Menthol2.8%................................Cough Suppressant and topical analgesic

Active ingredient Purpose
Camphor 5.2%.............................Cough Suppressant and topical analgesic
Eucalyptus oil 1.2%......................Cough Suppressant
Menthol2.8%................................Cough Suppressant and topical analgesic
Uses
- on chest and throat, temporarily relieves cough due to common cold
- On muscles and joints, temporarily relieves minor aches and pains

Keep out of reach of children. If swallowed, get
medical help or contact a Poison Control Center right away.

INDICATIONS AND USAGE

Uses - temporarily relieves cough due to minor throat
and bronchial irritation associated with a cold.

Warnings
For external use only; avoid contact with the eyes.
Do not use
- by mouth - with tight bandages - in nostrils - on wounds or damaged skin
Ask a doctor before use if you have
- cough that occurs with too much phlegm (mucus)
- persistent or chronic cough such as occurs with smoking, asthma or emphysema.
When using this product, do not
- heat - microwave - add to hot water or any container
where heating water.May cause splattering and
result in burns.
Stop use and ask a doctor if
-muscle aches and pains persist for more than 7 days or come back
- cough lasts for more than 7 days, comes back or occurs with fever, rash or
persistent headache. These could be signs of a serious condition.
If pregnant or breast feeding, ask a professional before use.
Keep out of reach of children. If swallowed, get
medical help or contact a Poison Control Center right away.

Directions
- See Important warnings under "When using this
product"
- Adults and children 2 years and older:
- rub a thick layer on chest and throat or rub on sore aching muscles
- cover with a warm, dry cloth if desired
- keep clothing loose about throat/chest to help vapors reach the nose/mouth
- repeat up to three times per 24 hours or as directed by a doctor.
Children under 2 years of age" ask a doctor.
Other Information
store at room temperature

Inactive Ingredients
Carbomer 954, cedarleaf oil, cetyl alcohol,
cetyl palmitate, cyclomethicone copolyol,
dimethicone copolyol, dimethicone, ETDA,
glycerin, imidazolidinyl urea, isopropyl palmitate,
methylparaben, nutmeg oil, PEG-100 stearate,
propylparaben, purified water, sodium hydroxide,
stearic acid, thymol, titanium dioxide,
turpentine oil